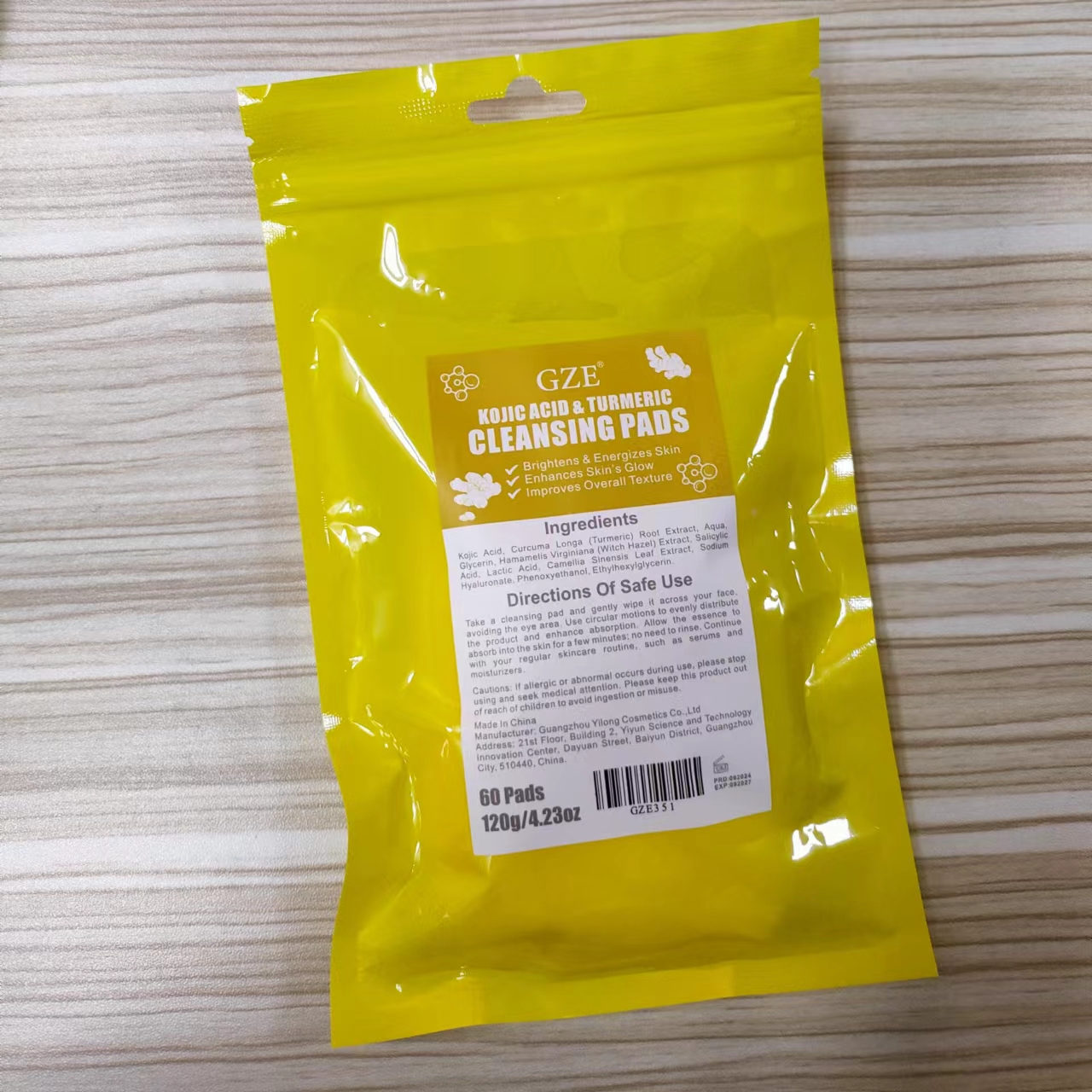 DRUG LABEL: GZE KOJIC ACID TURMERIC CLEANSING PADS
NDC: 74458-351 | Form: PATCH
Manufacturer: Guangzhou Yilong Cosmetics Co., Ltd
Category: otc | Type: HUMAN OTC DRUG LABEL
Date: 20241109

ACTIVE INGREDIENTS: KOJIC ACID 0.8 g/100 g; LACTIC ACID 7 g/100 g; SALICYLIC ACID 1.5 g/100 g
INACTIVE INGREDIENTS: PHENOXYETHANOL; GLYCERIN; ETHYLHEXYLGLYCERIN; GREEN TEA LEAF; CURCUMA LONGA (TURMERIC) ROOT EXTRACT; WITCH HAZEL; SODIUM HYALURONATE; AQUA

GZE KOJIC ACID TURMERIC CLEANSING PADS

ACTIVE INGREDIENT

Kojic Acid

Salicylic Acid

Lactic Acid

INACTIVE INGREDIENT

Curcuma Longa (Turmeric) Root Extract

Aqua

Glycerin

Hamamelis Virginiana (Witch Hazel) Extract

Camellia Sinensis Leaf Extract

Sodium Hyaluronate

Phenoxyethanol

Ethylhexylglycerin

INDICATIONS AND USAGE

Take a cleansing pad and gently wipe it across your face, avoiding the eye area. Use circular motions to evenly distribute the product and enhance absorption. Allow the essence to absorb into the skin for a few minutes; no need to rinse. Continue with your regular skincare routine, such as serums and moisturizers.

PURPOSE

Exfoliating.

DO NOT USE

1. Do not use on damaged or broken skin.

Stop use and ask a doctor if rash occurs.

WARNINGS

1. For external use only.

When using this product keep out of eyes. Rinse with water to remove.

Keep out of reach of children. If swallowed, get medical help or contact a Poison Control Center right away.

DOSAGE AND ADMINISTRATION

Take a cleansing pad and gently wipe it across your face, avoiding the eye area. Use circular motions to evenly distribute the product and enhance absorption. Allow the essence to absorb into the skin for a few minutes; no need to rinse. Continue with your regular skincare routine, such as serums and moisturizers.